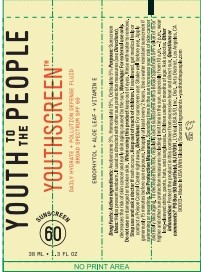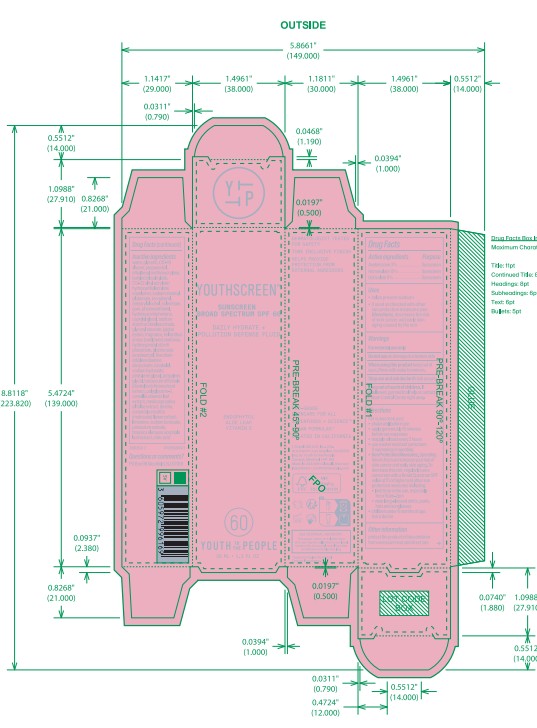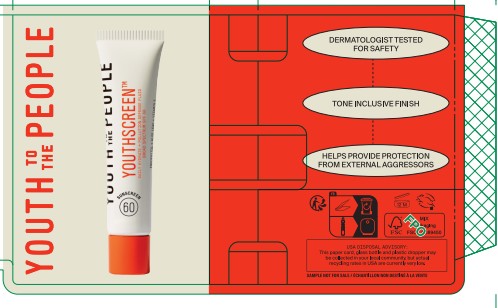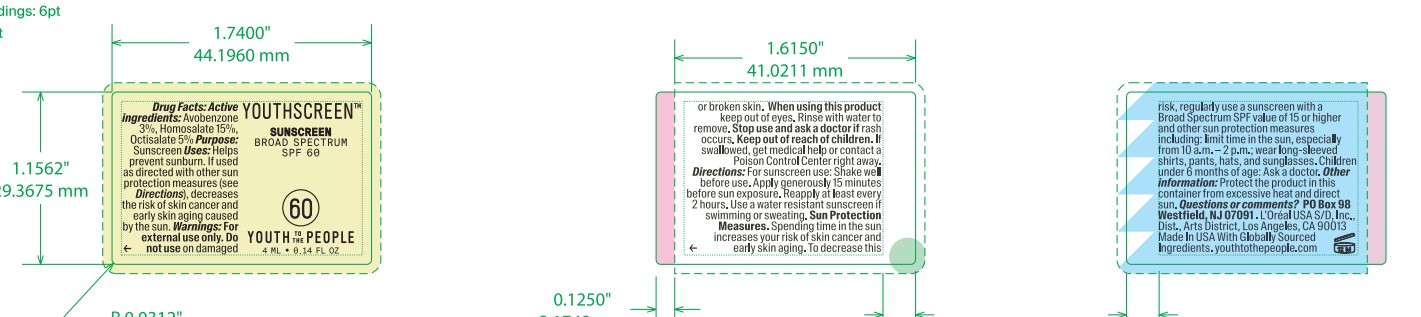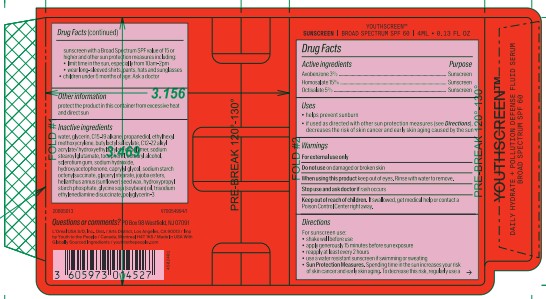 DRUG LABEL: Youth to the People Youthscreen Sunscreen Broad Spectrum SPF 60
NDC: 49967-169 | Form: CREAM
Manufacturer: L’Oreal USA Products Inc
Category: otc | Type: HUMAN OTC DRUG LABEL
Date: 20250630

ACTIVE INGREDIENTS: AVOBENZONE 30 mg/1 mL; HOMOSALATE 150 mg/1 mL; OCTISALATE 50 mg/1 mL
INACTIVE INGREDIENTS: WATER; GLYCERIN; C15-19 ALKANE; PROPANEDIOL; ETHYLHEXYL METHOXYCRYLENE; BUTYLOCTYL SALICYLATE; SODIUM STEAROYL GLUTAMATE; TOCOPHEROL; CETEARYL ALCOHOL; SCLEROTIUM GUM; SODIUM HYDROXIDE; PHENOXYETHANOL; HYDROXYACETOPHENONE; CAPRYLYL GLYCOL; GLYCERYL STEARATE; HELIANTHUS ANNUUS (SUNFLOWER) SEED WAX; SOYBEAN OIL; TRISODIUM ETHYLENEDIAMINE DISUCCINATE; BISABOLOL; PENTYLENE GLYCOL; PROPYLENE GLYCOL; TARAXACUM OFFICINALE ROOT; POLYGLYCERIN-3; GREEN TEA LEAF; MEDICAGO SATIVA WHOLE; CHAMOMILE; LIMONENE, (+)-; SODIUM BENZOATE; POTASSIUM SORBATE; KALE; CITRIC ACID

Drug Facts

Active ingredients

Avobenzone 3%

Homosalate 15%

Octisalate 5%

Purpose

Sunscreen

Uses

- helps prevent sunburn
- if used as directed with other sun protection measures (see Directions), decreases the risk of skin cancer and early skin aging caused by the sun

Warnings

For external use only

Do not use

on damaged or broken skin

When using this product

keep out of eyes. Rinse with water to remove.

Stop use and ask a doctor if

rash occurs

Keep out of reach of children.

If swallowed, get medical help or contact a Poison Control Center right away.

Directions

For sunscreen use:

- shake well before use
- apply generously 15 minutes before sun exposure
- reapply at least every 2 hours
- use a water resistant sunscreen if swimming or sweating

Sun Protection Measures: Spending time in the sun increases your risk of skin cancer and early skin aging. To decrease this risk, regularly use a sunscreen with a Broad Spectrum SPF value of 15 or higher and other sun protection measures including:

- limit time in the sun, especially from 10 a.m. - 2 p.m
- wear long-sleeved shirts, pants, hats, and sunglasses

- children under 6 months of age: Ask a doctor

Other information

protect the product in this container from excessive heat and direct sun

Inactive ingredients

water, glycerin, C15-19 alkane, propanediol, ethylhexyl methoxycrylene, butyloctyl salicylate, C12-22 alkyl acrylate/hydroxyethylacrylate copolymer, sodium stearoyl glutamate, tocopherol, cetearyl alcohol, sclerotium gum, sodium hydroxide, hydroxyacetophenone, caprylyl glycol, sodium starch octenylsuccinate, glyceryl stearate, jojoba esters, helianthus annus (sunflower) seed wax, hydroxypropyl starch phosphate, glycine soja (soybean) oil, trisodium ethylenediamine disuccinate, polyglycerin-3

Questions or comments?

PO Box 98 Westfield, NJ 07091